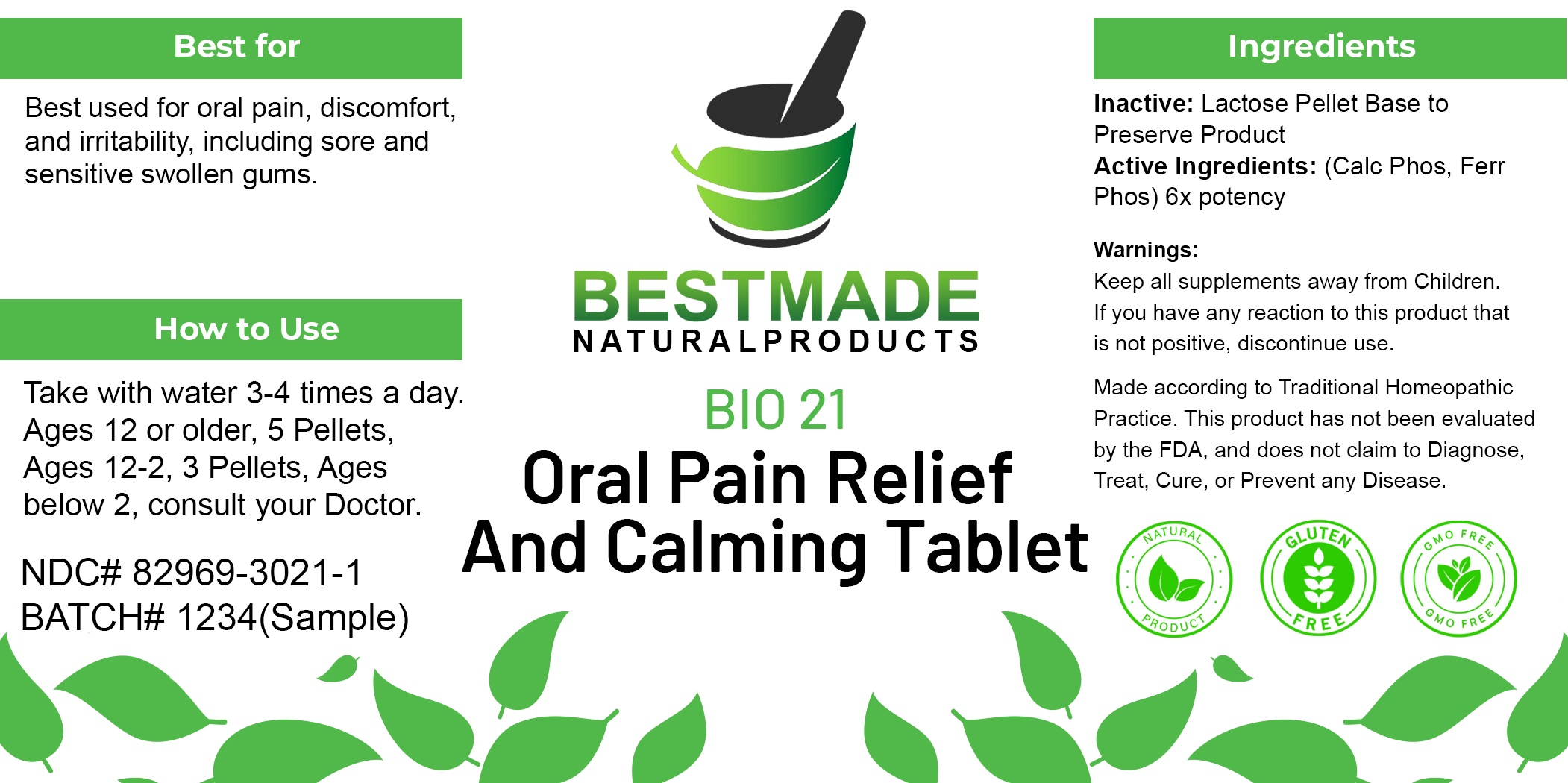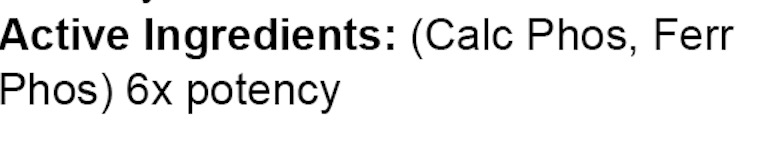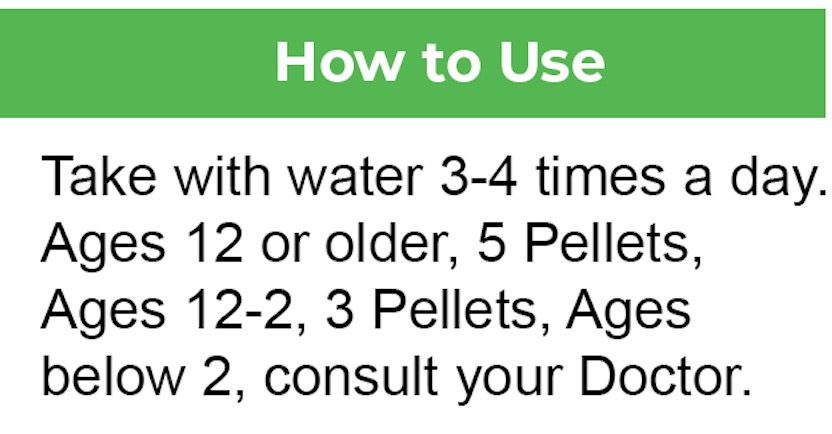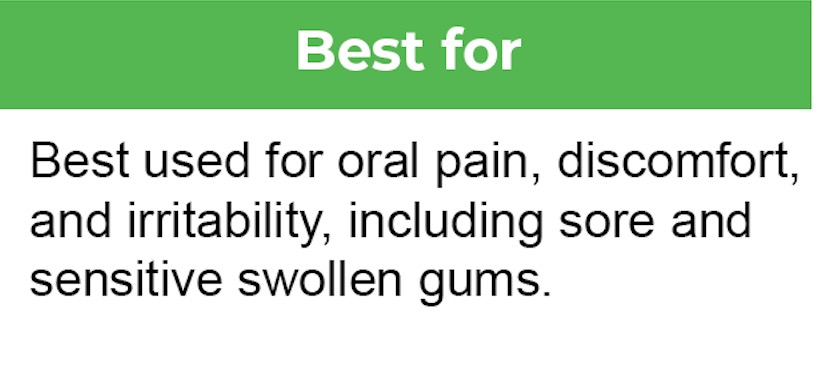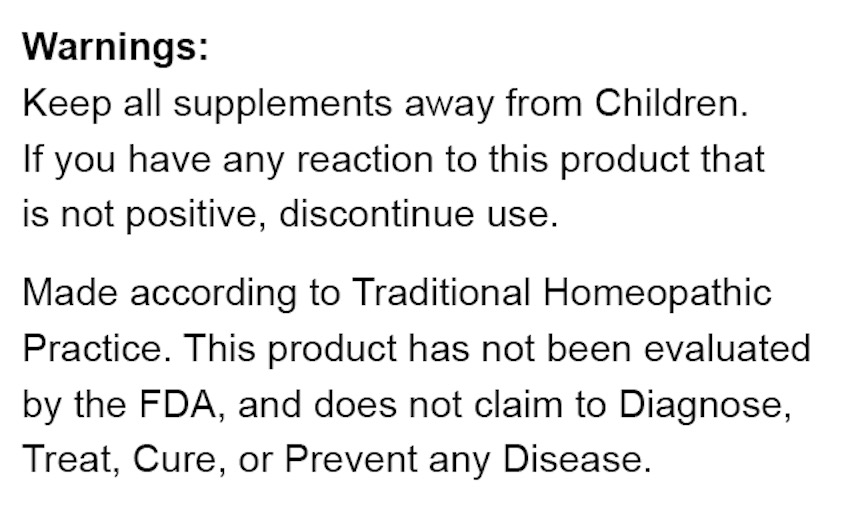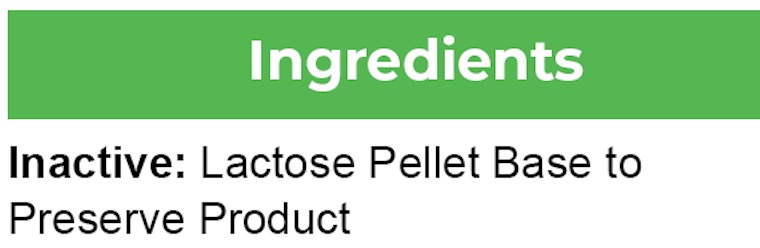 DRUG LABEL: Bestmade Natural Products Bio21
NDC: 82969-3021 | Form: TABLET, SOLUBLE
Manufacturer: Bestmade Natural Products
Category: homeopathic | Type: HUMAN OTC DRUG LABEL
Date: 20241217

ACTIVE INGREDIENTS: FERRIC PYROPHOSPHATE 6 [hp_X]/6 [hp_X]; CALCIUM PHOSPHATE 6 [hp_X]/6 [hp_X]
INACTIVE INGREDIENTS: LACTOSE, UNSPECIFIED FORM 6 [hp_X]/6 [hp_X]

DOSAGE AND ADMINISTRATION

How to Use
Take with water 3-4 times a day.
Ages 12 or older, 5 Pellets,
Ages 12-2, 3 Pellets, Ages
below 2, consult your Doctor.

INACTIVE INGREDIENT

Using a blank lactose pellet base to preserve and package and product.

INDICATIONS AND USAGE

Best used for oral pain, discomfort, and irritability, including sore and sensitive swollen gums.

ACTIVE INGREDIENT

(Calc Phos, Ferr Phos.)6x

Warnings:

Keep all supplements away from Children.

If you have any reaction to this product that is not positive, discontinue use.

Made according to Traditional Homeopathic Practice. This product has not been evaluated by the FDA, and does not claim to Diagnose, Treat, Cure, or Prevent any Disease.

PURPOSE

Best used for oral pain, discomfort, and irritability, including sore and sensitive swollen gums.

Warnings:

Keep all supplements away from Children.

If you have any reaction to this product that is not positive, discontinue use.

Made according to Traditional Homeopathic Practice. This product has not been evaluated by the FDA, and does not claim to Diagnose, Treat, Cure, or Prevent any Disease.

RECENT MAJOR CHANGES

Package label redesigned.

Entire package Label.